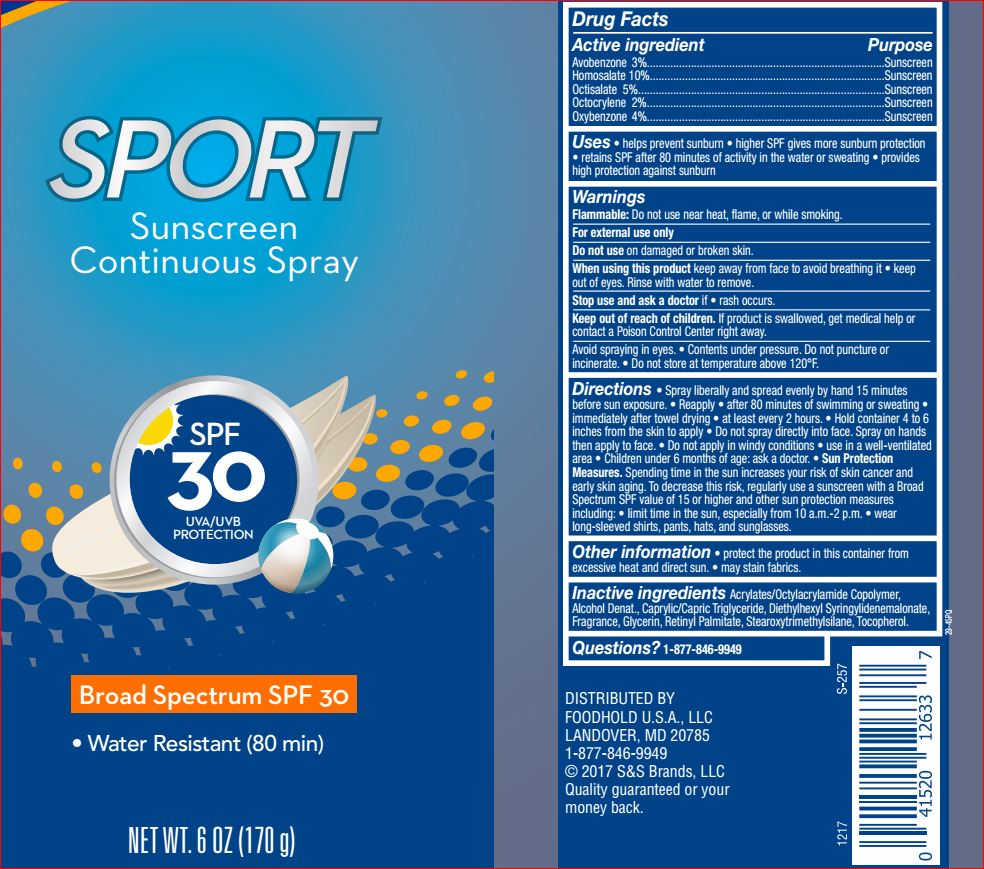 DRUG LABEL: Sport Sunscreen SPF 30
NDC: 41520-346 | Form: SPRAY
Manufacturer: Care One
Category: otc | Type: HUMAN OTC DRUG LABEL
Date: 20180710

ACTIVE INGREDIENTS: Avobenzone 3 g/100 g; Homosalate 10 g/100 g; Octisalate 5 g/100 g; Octocrylene 2 g/100 g; Oxybenzone 4 g/100 g
INACTIVE INGREDIENTS: ALCOHOL; MEDIUM-CHAIN TRIGLYCERIDES; Diethylhexyl Syringylidenemalonate; Glycerin; VITAMIN A PALMITATE; Stearoxytrimethylsilane; .ALPHA.-TOCOPHEROL ACETATE

Drug Facts

Active ingredients Purpose
Avobenzone 3.0%.........................................................................Sunscreen
Homosalate 10.0%........................................................................Sunscreen
Octisalate 5.0%............................................................................Sunscreen
Octocrylene 2.0%..........................................................................Sunscreen
Oxybenzone 4.0%.........................................................................Sunscreen

INDICATIONS AND USAGE

Uses • helps prevent sunburn • higher SPF gives more sunburn protection
• retains SPF after 80 minutes of activity in the water or sweating • provides high
protection against sunburn

Warnings
For external use only
Flammable: Do not use near heat, flame, or while smoking.
Do not use on damaged or broken skin
When using this product • Keep out of eyes. Rinse eyes with water to remove.
• Keep away from face to avoid breathing it • Do not puncture or incinerate. Contents under
pressure. Do not store at temperatures above 120ºF.
Stop use and ask a doctor if rash occurs

Directions
• Spray liberally and spread evenly by hand 15 minutes before sun exposure • Reapply: •
after 80 minutes of swimming or sweating • immediately after towel drying • at least every 2
hours • Hold container 4 to 6 inches from the skin to apply • Do not spray directly into face.
Spray on hands then apply to face. • Do not apply in windy conditions • use in a
well-ventilated area • Sun Protection Measures. Spending time in the
sun increases your risk of skin cancer and early skin aging. To decrease
this risk, regularly use a sunscreen with a broad spectrum SPF of 15 or
higher and other sun protection measures including: • limit time in the
sun, especially from 10 a.m. – 2 p.m. • wear long-sleeve shirts, pants,
hats, and sunglasses • children under 6 months: Ask a doctor

Inactive ingredients

Acrylates/Octylacrylamide Copolymer,
Alcohol Denat., Caprylic/Capric Triglyceride, Diethylhexyl
Syringylidenemalonate, Fragrance, Glycerin, Retinyl Palmitate,
Stearoxytrimethylsilane, Tocopherol.

Questions? 21-877-846-9949